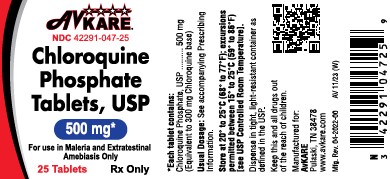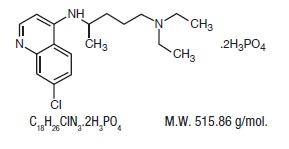 DRUG LABEL: Chloroquine Phosphate
NDC: 42291-047 | Form: TABLET
Manufacturer: AvKARE
Category: prescription | Type: HUMAN PRESCRIPTION DRUG LABEL
Date: 20260113

ACTIVE INGREDIENTS: CHLOROQUINE PHOSPHATE 500 mg/1 1
INACTIVE INGREDIENTS: ANHYDROUS CITRIC ACID; HYDROGENATED COTTONSEED OIL; LACTOSE MONOHYDRATE; MAGNESIUM STEARATE; STARCH, CORN; STARCH, POTATO

Chloroquine Phosphate Tablets, USP
(500 mg)
Rx only

DESCRIPTION

Chloroquine phosphate tablet, USP, is a 4-aminoquinoline compound for oral administration. It is a white, crystalline powder, freely soluble in water, practically insoluble in alcohol (ethanol 96%), in chloroform and in ether.

Chloroquine phosphate tablet is an antimalarial and amebicidal drug.

Chemically, it is 7-chloro-4-[[4- (diethylamino)-1-methylbutyl]amino] quinoline phosphate (1:2) and has the following structural formula:

Each tablet contains 500 mg of chloroquine phosphate USP, equivalent to 300 mg chloroquine base.

Inactive Ingredients: Anhydrous citric acid, hydrogenated vegetable oil, lactose monohydrate, magnesium stearate, corn starch, pregelatinized starch and starch.

CLINICAL PHARMACOLOGY

Chloroquine is rapidly and almost completely absorbed from the gastrointestinal tract, and only a small proportion of the administered dose is found in the stools. Approximately 55% of the drug in the plasma is bound to nondiffusible plasma constituents. Excretion of chloroquine is quite slow but is increased by acidification of the urine. Chloroquine is deposited in the tissues in considerable amounts. In animals, from 200 to 700 times the plasma concentration may be found in the liver, spleen, kidney, and lung; leukocytes also concentrate the drug. The brain and spinal cord, in contrast, contain only 10 to 30 times the amount present in plasma.

Chloroquine undergoes appreciable degradation in the body. The main metabolite is desethylchloroquine, which accounts for one fourth of the total material appearing in the urine; bisdesethylchloroquine, a carboxylic acid derivative, and other metabolic products as yet uncharacterized are found in small amounts. Slightly more than half of the urinary drug products can be accounted for as unchanged chloroquine.

Cardiac Electrophysiology

QTc interval prolongation was studied in a randomized, placebo-controlled parallel trial in 116 healthy subjects who received either chloroquine (1,000 mg) alone or in combination with oral azithromycin (500 mg, 1,000 mg, and 1,500 mg once daily). Co-administration of azithromycin increased the QTc interval in a dose- and concentration- dependent manner. In comparison to chloroquine alone, the maximum mean (95% upper confidence bound) increases in QTcF were 5 ms, 7 (12) ms and 9 (14) ms with the co-administration of 500 mg, 1,000 mg and 1,500 mg azithromycin, respectively.

Microbiology

Mechanism of Action: Chloroquine, a 4-aminoquinoline, is an anti-protozoal agent. The precise mechanism by which chloroquine exhibits activity is not known. Chloroquine, may exert its effect against Plasmodiumspecies by concentrating in the acid vesicles of the parasite and by inhibiting polymerization of heme. It can also inhibit certain enzymes by its interaction with DNA.

Activity in Vitroand in Clinical Infections: Chloroquine is active against the erythrocytic forms of susceptible strains of Plasmodium falciparum, Plasmodium malariae, Plasmodium ovale,and Plasmodium vivax. Chloroquine is not active against the gametocytes and the exoerythrocytic forms including the hypnozoite stage (P. vivaxand P. ovale) of the Plasmodiumparasites.

In vitrostudies with Chloroquine demonstrated that it is active against the trophozoites of Entamoeba histolytica.

Drug Resistance: Resistance of Plasmodiumparasites to chloroquine is widespread (see INDICATIONS AND USAGE, Limitations of Use in Malariaand WARNINGS).

Plasmodiumparasites exhibiting reduced susceptibility to hydroxychloroquine also show reduced susceptibility to chloroquine.

Patients in whom chloroquine or hydroxychloroquine have failed to prevent or cure clinical malaria or parasitemia, or patients who acquired malaria in a geographic area where chloroquine resistance is known to occur should be treated with another form of antimalarial therapy (see WARNINGSand INDICATIONS AND USAGE, Limitations of Use).

INDICATIONS AND USAGE

Chloroquine phosphate tablets are indicated for the:

- Treatment of uncomplicated malaria due to susceptible strains of P. falciparum, P.malariae, P. ovale, and P.vivax.
- Prophylaxis of malaria in geographic areas where resistance to chloroquine is not present.
- Treatment of extraintestinal amebiasis.

Chloroquine phosphate tablets do not prevent relapses in patients with vivax or ovale malaria because it is not effective against exoerythrocytic forms of the parasites.

Limitations of Use in Malaria:

- Do not use chloroquine phosphate tablets for the treatment of complicated malaria (high-grade parasitemia and/or complications e.g., cerebral malaria or acute renal failure).
- Do not use chloroquine phosphate tablets for malaria prophylaxis in areas where chloroquine resistance occurs, Resistance to chloroquine phosphate tablets are widespread in P. falciparum,and is reported in P.vivax(see WARNINGS).
- Concomitant therapy with an 8-aminoquinoline drug is necessary for treatment of the hypnozoite liver stage forms of P.vivaxand P.ovale(see DOSAGE AND ADMINISTRATION).

CONTRAINDICATIONS

Use of chloroquine phosphate tablets for indications other than acute malaria is contraindicated in the presence of retinal or visual field changes of any etiology.

Use of chloroquine phosphate tablets are contraindicated in patients with known hypersensitivity to 4-aminoquinoline compounds.

WARNINGS

Chloroquine-Resistant Malaria

Chloroquine phosphate tablets are not effective against chloroquine- or hydroxychloroquine-resistant strains of Plasmodiumspecies (see CLINICAL PHARMACOLOGY, Microbiology). Chloroquine resistance is widespread in P. falciparumand is reported in P. vivax.Before using chloroquine for prophylaxis, it should be ascertained whether chloroquine is appropriate for use in the region to be visited by the traveler. Information regarding the geographic areas where resistance to chloroquine occurs, is available at the Centers for Disease Control and Prevention (www.cdc.gov\malaria).

Patients infected with a resistant strain of plasmodia as shown by the fact that normally adequate doses have failed to prevent or cure clinical malaria or parasitemia should be treated with another form of antimalarial therapy.

Treatment of Exo-Erythrocytic Forms of Malaria

Chloroquine does not treat the hypnozoite liver stage forms of Plasmodiumand will therefore not prevent relapses of malaria due to P. vivaxor P. ovale.Additional treatment with an anti-malarial agent active against these forms, such as an 8-aminoquinoline, is required for the treatment of infections with P. vivaxand P. ovale.

Cardiac Effects including Cardiomyopathy and QT prolongation

Fatal and life-threatening cardiotoxicity, including cardiomyopathy and arrhythmias, have been reported with the use of chloroquine (see ADVERSE REACTIONSand OVERDOSAGE). In multiple cases, endomyocardial biopsy showed association of the cardiomyopathy with phospholipidosis in the absence of inflammation, infiltration, or necrosis. Patients may present with ventricular hypertrophy and conduction disorders. ECG findings include atrioventricular, right or left bundle branch block. Chronic toxicity should be considered when conduction disorders (bundle branch block / atrio-ventricular heart block) are diagnosed.

QT interval prolongation, torsades de pointes, and ventricular arrhythmias have been reported with the use of chloroquine. The risk is greater if chloroquine is administered at high doses. Chloroquine should be used with caution in patients with cardiac disease, a history of ventricular arrhythmias, uncorrected hypokalemia and/or hypomagnesemia, or bradycardia (˂ 50 bpm), and during concomitant administration with QT interval prolonging agents due to potential for QT interval prolongation (see WARNINGS, PRECAUTIONS, Drug Interactions, ADVERSE REACTIONSand OVERDOSAGE). Monitor for signs and symptoms of cardiotoxicity during chloroquine therapy. Discontinue chloroquine if cardiotoxicity is suspected or demonstrated by tissue biopsy.

Hypoglycemia

Chloroquine has been shown to cause severe hypoglycemia including loss of consciousness that could be life-threatening in patients treated with or without antidiabetic medications (see PRECAUTIONS, Drug Interactions). Patients treated with chloroquine phosphate tablets should be warned about the risk of hypoglycemia and the associated clinical signs and symptoms. Patients presenting with clinical symptoms suggestive of hypoglycemia during treatment with chloroquine should have their blood glucose level checked and treatment reviewed as necessary.

Retinopathy^1

Irreversible retinal damage has been observed in some patients who had received chloroquine. Significant risk factors for retinal damage include daily doses of chloroquine phosphate greater than 2.3 mg/kg of actual body weight, durations of use greater than five years, subnormal glomerular filtration, use of some concomitant drug products such as tamoxifen citrate (see PRECAUTIONS), and concurrent macular disease.

A baseline ophthalmological examination should be performed within the first year of starting chloroquine phosphate tablets. The baseline exam should include: best corrected distance visual acuity (BCVA), an automated threshold visual field (VF) of the central 10 degrees (with retesting if an abnormality is noted), and spectral domain optical coherence tomography (SD-OCT).

For individuals with significant risk factors (daily dose of chloroquine phosphate greater than 2.3 mg/kg of actual body weight, subnormal glomerular filtration, use of tamoxifen citrate or concurrent macular disease) monitoring should include annual examinations which include BCVA, VF and SD-OCT. For individuals without significant risk factors, annual exams (including BCVA, VF and SD-OCT) can usually be deferred until five years of treatment.

In individuals of Asian descent, retinal toxicity may first be noticed outside the macula. In patients of Asian descent, it is recommended that visual field testing be performed in the central 24 degrees instead of the central 10 degrees.

It is recommended that chloroquine be discontinued if ocular toxicity is suspected and the patient should be closely observed given that retinal changes (and visual disturbances) may progress even after cessation of therapy.

Central Nervous System Effects

Acute extrapyramidal disorders may occur with chloroquine (see PRECAUTIONS, ADVERSE REACTIONSand OVERDOSAGE). These adverse reactions usually resolve after treatment discontinuation and/or symptomatic treatment.

Skeletal Muscle Myopathy and Neuropathy

Skeletal muscle myopathy or neuropathy leading to progressive weakness and atrophy of proximal muscle groups, and abnormal nerve conduction, have been reported. Muscle and nerve biopsies have shown associated phospholipidosis. Assess muscle strength and deep tendon reflexes periodically in patients on long-term therapy with chloroquine. Discontinue chloroquine if muscle or nerve toxicity is suspected or demonstrated by tissue biopsy.

Renal Toxicity

Proteinuria with or without a moderate reduction in glomerular filtration rate have been reported with the use of chloroquine. Renal biopsy showed phospholipidosis without immune deposits, inflammation, and/or increased cellularity. Physicians should consider phospholipidosis as a possible cause of renal injury in patients with underlying connective tissue disorders who are receiving chloroquine. Discontinue chloroquine if renal toxicity is suspected or demonstrated by tissue biopsy.

Pediatric Accidental Ingestion

A number of fatalities have been reported following the accidental ingestion of chloroquine, sometimes in relatively small doses (0.75 g or 1 g chloroquine phosphate in one 3-year-old child). Patients should be strongly warned to keep chloroquine phosphate tablets out of the reach of children because they are especially sensitive to the 4-aminoquinoline compounds (see OVERDOSAGEand ADVERSE REACTIONS).

Worsening of Psoriasis and Porphyria

Use of chloroquine phosphate tablets in patients with psoriasis may precipitate a severe attack of psoriasis. When used in patients with porphyria the condition may be exacerbated. Chloroquine phosphate tablets should not be used in these conditions unless the benefit to the patient outweighs the potential risks.

Potential Carcinogenic Risk

Experimental data showed a potential risk of inducing gene mutations. There is insufficient evidence regarding the carcinogenicity of chloroquine in experimental animals (see PRECAUTIONS, Carcinogenesis, Mutagenesis, Impairment of Fertility). In humans, there are insufficient data to rule out an increased risk of cancer in patients receiving long-term treatment.

Usage in Pregnancy

In animal studies, embryo-fetal developmental toxicity was shown at doses ranging from 250 mg/kg to 1,500 mg/kg body weight; approximately 3 to 16 times the maximum recommended therapeutic dose based on a body surface area comparison (see PRECAUTIONS, Animal Pharmacology and/or Animal Toxicology). Preclinical data showed a potential risk of genotoxicity in some test systems (PRECAUTIONS, Carcinogenesis, Mutagenesis, Impairment of Fertility).

In humans, at recommended doses for prophylaxis and treatment of malaria, observational studies as well as a meta-analysis, including a small number of prospective studies with chloroquine exposure during pregnancy, have shown no increase in the rate of birth defects or spontaneous abortions.

The individual benefit-risk balance should be reviewed before prescribing chloroquine in pregnant women.

PRECAUTIONS

Hematological Effects/Laboratory Tests

Complete blood cell counts should be checked periodically if patients are given prolonged therapy (see ADVERSE REACTIONS).

Chloroquine may cause hemolysis in glucose-6 phosphate dehydrogenase (G-6-PD) deficiency. Blood monitoring may be needed as hemolytic anemia may occur, in particular in association with other drugs that cause hemolysis (see ADVERSE REACTIONS).

Auditory Effects

In patients with preexisting auditory damage, chloroquine should be administered with caution. In case of any defects in hearing, chloroquine should be immediately discontinued, and the patient closely observed (see ADVERSE REACTIONS).

Use in Patients with Hepatic Impairment

Since chloroquine phosphate tablets are known to concentrate in the liver, it should be used with caution in patients with hepatic disease or alcoholism or in conjunction with known hepatotoxic drugs.

Central Nervous System Effects

Chloroquine may increase the risk of convulsions in patients with a history of epilepsy.

Drug Interactions

Antacids and kaolin: Antacids and kaolin can reduce absorption of chloroquine; an interval of at least 4 hours between intake of these agents and chloroquine should be observed.

Cimetidine: Cimetidine can inhibit the metabolism of chloroquine, increasing its plasma level. Concomitant use of cimetidine should be avoided.

Insulin and other antidiabetic drugs: As chloroquine may enhance the effects of a hypoglycemic treatment, a decrease in doses of insulin or other antidiabetic drugs may be required.

Arrhythmogenic drugs: There may be an increased risk of inducing ventricular arrhythmias if chloroquine is used concomitantly with other arrhythmogenic drugs, such as amiodarone or moxifloxacin.

Ampicillin: In a study of healthy volunteers, chloroquine significantly reduced the bioavailability of ampicillin. An interval of at least two hours between intake of ampicillin and chloroquine should be observed.

Cyclosporine: After introduction of chloroquine (oral form), a sudden increase in serum cyclosporine level has been reported. Therefore, close monitoring of serum cyclosporine level is recommended and, if necessary, chloroquine should be discontinued.

Mefloquine: Co-administration of chloroquine and mefloquine may increase the risk of convulsions.

The blood concentrations of chloroquine and desethylchloroquine (the major metabolite of chloroquine, which also has antimalarial properties) were negatively associated with log antibody titers. Chloroquine taken in the dose recommended for malaria prophylaxis can reduce the antibody response to primary immunization with intradermal human diploid-cell rabies vaccine.

Praziquantel: In a single-dose interaction study, chloroquine has been reported to reduce the bioavailability of praziquantel.

Tamoxifen: Concomitant use of chloroquine with drugs known to induce retinal toxicity such as tamoxifen is not recommended (see WARNINGS).

Carcinogenesis, Mutagenesis, Impairment of Fertility

Carcinogenesis

There is insufficient evidence regarding the carcinogenicity of chloroquine in experimental animals.

Mutagenesis

Chloroquine is reported in the literature to be a weak genotoxic agent which may elicit both gene mutations and chromosomal/DNA breaks. Mechanisms may involve DNA intercalation or induction of oxidative stress. The publications reported both positive and negative results in the in vitroreverse gene mutation assays using bacteria (Ames test) and in the in vivostudies using rodents (mouse bone marrow cell sister chromatid exchange, mouse bone marrow cell chromosome abnormality, and rat DNA strand breaks in multiple organs when animals were dosed by intraperitoneal route). Those chromosomal effects were not observed when chloroquine was administered in animals orally (i.e. the therapeutic route of administration). Altogether those cellular and rodent data show evidence of genotoxic potential but discrepancies have been noted between published data.

Fertility

A study in male rats after 30 days of oral treatment at 5 mg/day of chloroquine showed a decrease in testosterone levels, weight of testes, epididymis, seminal vesicles, and prostate. Untreated female rats had reduced number of fetuses after mating with males that received intraperitoneal injections of 10 mg/kg chloroquine for 14 days.

Animal Pharmacology and/or Animal Toxicology

Based on non-Good Laboratory Practice literature reports, chloroquine causes malformations in rats, resulting in a fetal mortality rate of 25% after administration at doses between 250 mg/kg and 1,500 mg/kg (approximately 3 to 16 times the maximum recommended therapeutic dose of 900 mg of chloroquine base, based on a body surface area comparison), showing ocular malformations in 45% of fetuses in the 1,000 mg/kg group (approximately 11 times the maximum recommended therapeutic dose based on a body surface area comparison). Autoradiographic studies have shown that when administered at the start or the end of gestation, chloroquine accumulates in the eyes and ears.

Pregnancy

See WARNINGS, Usage in Pregnancy.

Nursing Mothers

Because of the potential for serious adverse reactions in nursing infants from chloroquine, a decision should be made whether to discontinue nursing or to discontinue the drug, taking into account the potential clinical benefit of the drug to the mother.

The excretion of chloroquine and the major metabolite, desethylchloroquine, in breast milk was investigated in eleven lactating mothers following a single oral dose of chloroquine (600 mg base). The maximum daily dose of the drug that the infant can receive from breastfeeding was about 0.7% of the maternal start dose of the drug in malaria chemotherapy. Separate chemoprophylaxis for the infant is required (see DOSAGE AND ADMINISTRATION).

Pediatric Use

See WARNINGSand DOSAGE AND ADMINISTRATION.

Geriatric Use

Clinical studies of chloroquine phosphate tablets did not include sufficient numbers of subjects aged 65 and over to determine whether they respond differently from younger subjects. However, this drug is known to be substantially excreted by the kidney, and the risk of toxic reactions to this drug may be greater in patients with impaired renal function. Because elderly patients are more likely to have decreased renal function, care should be taken in dose selection and it may be useful to monitor renal function.

ADVERSE REACTIONS

The following adverse reactions have been identified during post-approval use of chloroquine or other 4-aminoqunoline compounds. Because these reactions are reported voluntarily from a population of uncertain size, it is not always possible to reliably estimate their frequency or establish a causal relationship to drug exposure.

Ocular disorders:Maculopathy and macular degeneration have been reported and may be irreversible. Irreversible retinopathy with retinal pigmentation changes (bull’s eye appearance) and visual field defects (paracentral scotomas) in patients receiving long-term or high-dosage 4- aminoquinoline therapy have been reported (see WARNINGS). Visual disturbances (blurring of vision and difficulty of focusing or accommodation); nyctalopia; scotomatous vision with field defects of paracentral, pericentral ring types, and typically temporal scotomas (e.g., difficulty in reading with words tending to disappear, seeing half an object, misty vision, and fog before the eyes) have been reported. Reversible corneal opacities have also been reported.

Immune system disorders:Urticaria, anaphylactic reaction including angioedema.

Ear and labyrinth disorders:Nerve type deafness; tinnitus, reduced hearing in patients with preexisting auditory damage.

Musculoskeletal and connective tissue-disorders:Sensorimotor disorders, skeletal muscle myopathy or neuromyopathy leading to progressive weakness and atrophy of proximal muscle groups, depression of tendon reflexes and abnormal nerve conduction.

Gastrointestinal disorders:Hepatitis, increased liver enzymes, anorexia, nausea, vomiting, diarrhea, abdominal cramps.

Skin and subcutaneous tissue disorders:Erythema multiforme, Stevens-Johnson syndrome, toxic epidermal necrolysis, exfoliative dermatitis. Pleomorphic skin eruptions, skin and mucosal pigmentary changes; lichen planus-like eruptions, pruritus,; drug rash with eosinophilia and systemic symptoms (DRESS syndrome); photosensitivity and hair loss and bleaching of hair pigment.

Blood and lymphatic system disorders:Pancytopenia, aplastic anemia, reversible agranulocytosis, thrombocytopenia and neutropenia. Hemolytic anemia in G6PD deficient patients (see PRECAUTIONS).

Nervous system disorders:Convulsions, mild and transient headache, polyneuropathy, acute extrapyramidal disorders (such as dystonia, dyskinesia, tongue protrusion, torticollis) (see WARNINGSand OVERDOSAGE).

Neuropsychiatric disorders:Neuropsychiatric changes including psychosis, delirium, anxiety, agitation, insomnia, confusion, hallucinations, personality changes, depression, and suicidal behavior.

Cardiac disorders:Hypotension, electrocardiographic changes (particularly, inversion or depression of the T-wave with widening of the QRS complex), and cardiomyopathy (which may result in cardiac failure and in some cases a fatal outcome).

Cardiac arrhythmias, conduction disorders such as bundle branch block / atrio-ventricular block, QT interval prolongation, torsade de pointes, ventricular tachycardia and ventricular fibrillation have been reported with therapeutic doses of chloroquine as well as with overdose. The risk is greater if chloroquine is administered at high doses. Fatal cases have been reported (see WARNINGS, Cardiac Effectsand OVERDOSAGE).

Metabolic and Nutritional disorders:Hypoglycemia (see WARNINGS).

To report SUSPECTED ADVERSE REACTIONS, contact AvKARE at 1-855-361-3993 or FDA at 1-800-FDA-1088 or www.fda.gov/medwatch.

OVERDOSAGE

Signs and Symptoms:Chloroquine is very rapidly and completely absorbed after ingestion. Toxic doses of chloroquine can be fatal. As little as 1 g may be fatal in children. Toxic symptoms can occur within minutes. The symptoms of overdosage may include nausea, vomiting, headache, drowsiness, visual disturbances, cardiovascular collapse, convulsions, hypokalemia, rhythm and conduction disorders including QT prolongation, torsades de pointes, ventricular tachycardia and ventricular fibrillation, followed by sudden potentially fatal respiratory and cardiac arrest. Immediate medical attention is required, as these effects may appear shortly after the overdose. Cases of extrapyramidal disorders have also been reported in the context of chloroquine overdose (see WARNINGSand ADVERSE REACTIONS).

Treatment:Treatment is symptomatic and must be prompt with immediate evacuation of the stomach by emesis or gastric lavage followed by treatment with activated charcoal. Chloroquine overdose is a life-threatening emergency and should be managed with cardio-respiratory and hemodynamic support, monitoring of potassium along with management of arrhythmias and convulsions, as necessary. A patient who survives the acute phase and is asymptomatic should be closely observed until all clinical features of toxicity resolve.

DOSAGE AND ADMINISTRATION

The dosage of chloroquine phosphate is often expressed in terms of equivalent chloroquine base. Each 500 mg tablet of chloroquine phosphate tablet contains the equivalent of 300 mg chloroquine base. In infants and children the dosage is preferably calculated by body weight.

Prophylaxis against chloroquine-sensitive Plasmodiumspecies

Adult Dose:The dosage for prophylaxis is 500 mg (= 300 mg base) administered once per week on exactly the same day of each week.

Pediatric Dose:The dosage for prophylaxis is 5 mg calculated as base, per kg of body weight, administered once per week on exactly the same day of each week. The pediatric dose should never exceed the adult dose regardless of weight.

If circumstances permit, suppressive therapy should begin two weeks prior to exposure. However, failing this in adults, an initial double (loading) dose of 1 g (= 600 mg base), or in children 10 mg base/kg may be taken in two divided doses, six hours apart. The suppressive therapy should be continued for eight weeks after leaving the endemic area.

Treatment of uncomplicated malaria due to chloroquine-sensitive Plasmodiumspecies

Adults:An initial dose of 1 g salt (= 600 mg base) followed by an additional 500 mg (= 300 mg base) after six to eight hours and a single dose of 500 mg (= 300 mg base) on each of two consecutive days. This represents a total dose of 2.5 g chloroquine phosphate or 1.5 g base in three days.

Infants and Children:In infants and children, the recommended dose is 10 mg base/kg followed by 5 mg based/kg at 6, 24 and 36 hours (total dose 25 mg based/kg). The pediatric dose should never exceed the adult dose regardless of weight.

The dosage for adults of low body weight and for infants and children should be determined as follows:

First dose: 10 mg base per kg (but not exceeding a single dose of 600 mg base).

Second dose: (6 hours after first dose) 5 mg base per kg (but not exceeding a single dose of 300 mg base).

Third dose: (24 hours after first dose) 5 mg base per kg.

Fourth dose: (36 hours after first dose) 5 mg base per kg.

P. vivaxand P. ovale:Concomitant therapy with an 8-aminoquinoline compound is necessary for treatment of the hypnozoite liver stage forms of the parasites.

Extraintestinal Amebiasis: Adults Dosage:1 g salt (600 mg base) daily for two days, followed by 500 mg (300 mg base) daily for at least two to three weeks. Treatment is usually combined with an effective intestinal amebicide.

Geriatric Use

See PRECAUTIONS, Geriatric Use.

HOW SUPPLIED

Chloroquine Phosphate Tablets USP, 500 mg, equivalent to 300 mg of chloroquine base are supplied as white to off-white, round tablets, debossed with "7010" on one side and plain on the other side.

They are available as follows:

Bottles of 25: NDC 42291-047-25

Dispense in tight, light-resistant container as defined in the USP.

Store at 20° to 25°C (68° to 77°F); excursions permitted between 15° to 30°C (59° to 86°F) [see USP Controlled Room Temperature]

REFERENCES

1. Marmor MF, Kellner U, and Lai TY, et al. Recommendations on Screening for Chloroquine and Hydroxychloroquine Retinopathy (2016 Revision). Ophthalmology 2016. Doi10.1016/jophtha.2016.01.058

Manufactured for:

AvKARE

Pulaski, TN 38478

Mfg. Rev. 05-2022-01

AV 11/23 (M)